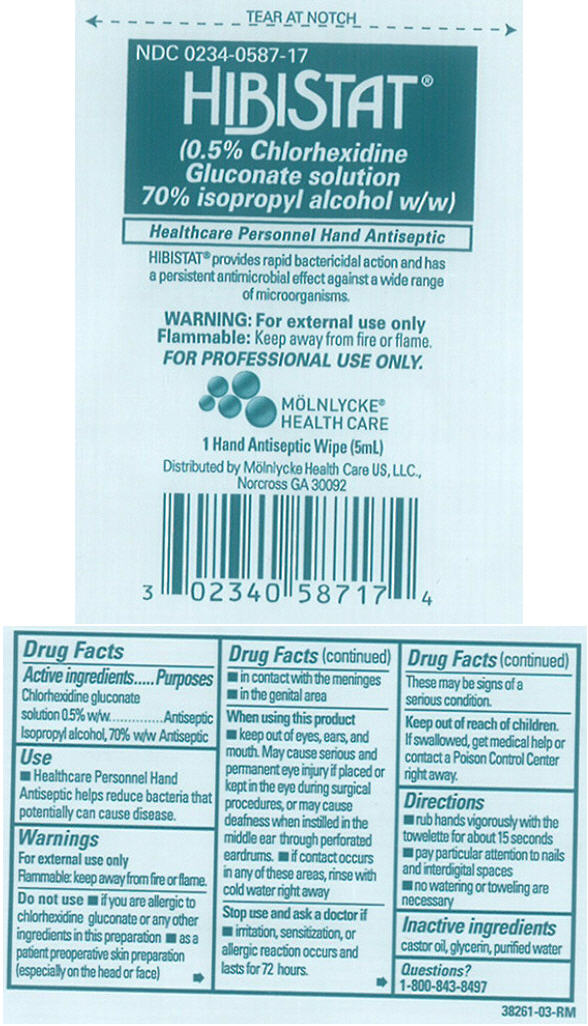 DRUG LABEL: Hibistat
NDC: 0234-0587 | Form: SOLUTION
Manufacturer: Mölnlycke Health Care US, LLC
Category: otc | Type: HUMAN OTC DRUG LABEL
Date: 20110419

ACTIVE INGREDIENTS: Chlorhexidine gluconate 0.525 g/5 mL; Isopropyl alcohol 70 g/5 mL
INACTIVE INGREDIENTS: Castor Oil; Glycerin; Water

HIBISTAT®
(0.5% Chlorhexidine
Gluconate solution
70% isopropyl alcohol w/w)

Drug Facts

ACTIVE INGREDIENT

PURPOSE

Active ingredients | Purposes
Chlorhexidine gluconate solution 0.5% w/w | Antiseptic
Isopropyl alcohol, 70% w/w | Antiseptic

Use

- Healthcare Personnel Hand Antiseptic helps reduce bacteria that potentially can cause disease.

Warnings

For external use only

Flammable: keep away from fire or flame.

Do not use

- if you are allergic to chlorhexidine gluconate or any other ingredients in this preparation
- as a patient preoperative skin preparation (especially on the head or face)
- in contact with the meninges
- in the genital area

When using this product

- keep out of eyes, ears, and mouth. May cause serious and permanent eye injury if placed or kept in the eye during surgical procedures, or may cause deafness when instilled in the middle ear through perforated eardrums.
- if contact occurs in any of these areas, rinse with cold water right away

Stop use and ask a doctor if

- irritation, sensitization, or allergic reaction occurs and lasts for 72 hours. These may be signs of a serious condition.

Keep out of reach of children. If swallowed, get medical help or contact a Poison Control Center right away.

Directions

- rub hands vigorously with the towelette for about 15 seconds
- pay particular attention to nails and interdigital spaces
- no watering or toweling are necessary

Inactive ingredients

castor oil, glycerin, purified water

Questions?

1-800-843-8497

PRINCIPAL DISPLAY PANEL - 5mL Wipe Packet

NDC 0234-0587-17

HIBISTAT®
(0.5% Chlorhexidine
Gluconate solution
70% isopropyl alcohol w/w)

Healthcare Personnel Hand Antiseptic

HIBISTAT® provides rapid bactericidal action and has
a persistent antimicrobial effect against a wide range
of microorganisms.

WARNING: For external use only
Flammable: Keep away from fire or flame.
FOR PROFESSIONAL USE ONLY.

MÖLNLYCKE®
HEALTH CARE

1 Hand Antiseptic Wipe (5mL)

Distributed by Mölnlycke Health Care US, LLC.,
Norcross GA 30092